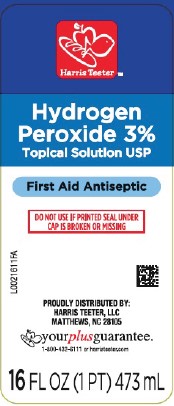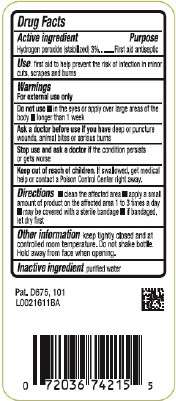 DRUG LABEL: Hydrogen Peroxide
NDC: 72036-871 | Form: SOLUTION
Manufacturer: HARRIS TEETER
Category: otc | Type: HUMAN OTC DRUG LABEL
Date: 20260204

ACTIVE INGREDIENTS: HYDROGEN PEROXIDE 30 mg/1 mL
INACTIVE INGREDIENTS: WATER

Harris Teeter 871.001/871AA
3% Hydrogen Peroxide

Active ingredient

Hydrogen peroxide (stablized) 3%

Purpose

First aid antiseptic

Use

- first aid to help prevent the risk of infection in minor cuts, scrapes and burns

Warnings

For external use only

Do not use

- in the eyes or apply over large areas of the body
- longer than 1 week

Ask a doctor before use if you have

deep or puncture wounds, animal bites or serious burns

Stop use and ask a doctor if

the condition persists or gets worse

Keep out of reach of children.

If swallowed, get medical help or contact a Poison Control Center right away.

Directions

- clean the affected area
- apply a small amount of product on the affected area 1 to 3 times a day
- may be covered with a sterile bandage
- if bandaged, let dry first

Other information

keep tightly closed and at controlled room temperature. Do not shake bottle. Hold away from face when opening.

Inactive ingredient

purified water

Claim

Pat. D675, 101

Principal display panel

Harris Teeter ™

Hydrogen Peroxide 3%

Topical Solutioon USP

First Aid Antiseptic

DO NOT USE IF PRINTED SEAL UNDER CAP IS BROKEN OR MISSING

PROUDLY DISTRIBUTED BY:

HARRIS TEETER, LLC

MATTHEWS, NC 28105

yourplusguarantee

1-800-432-6111 or harristetter.com

16 FL OZ (1 PT) 473 mL